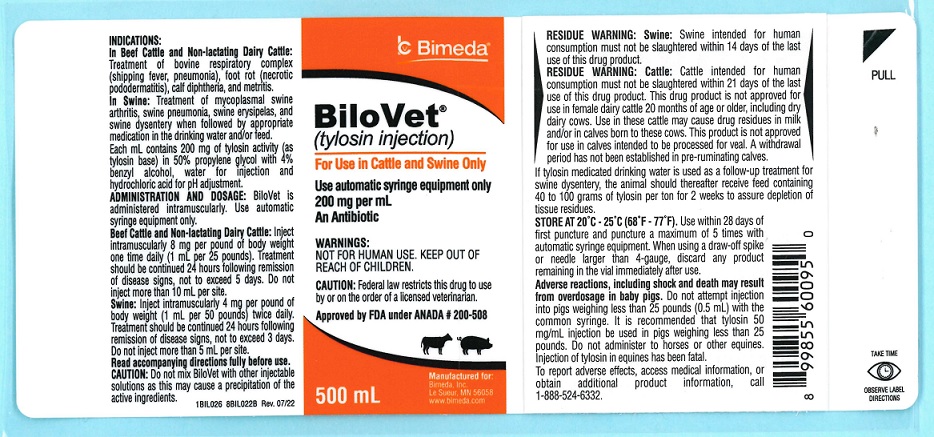 DRUG LABEL: BiloVet
NDC: 61133-4011 | Form: INJECTION, SOLUTION
Manufacturer: Bimeda, Inc.
Category: animal | Type: PRESCRIPTION ANIMAL DRUG LABEL
Date: 20241030

ACTIVE INGREDIENTS: TYLOSIN 200 mg/1 mL
INACTIVE INGREDIENTS: PROPYLENE GLYCOL; BENZYL ALCOHOL; water; HYDROCHLORIC ACID

BiloVet®
(tylosin injection)
For Use In Cattle and Swine Only
Use automatic syringe equipment only
200 mg per mL
An Antibiotic

DESCRIPTION

BiloVet®
(tylosin injection)

For Use in Cattle and Swine Only
Use automatic syringe equipment only
200 mg per mL
An Antibiotic

CAUTION: Federal law restricts this drug to use by or on the order of a licensed veterinarian.

INDICATIONS AND USAGE

INDICATIONS: In Beef Cattle and Non-lactating Dairy Cattle, BiloVet is indicated for use in the treatment of bovine respiratory complex (shipping fever, pneumonia) usually associated with Pasteurella multocida and Arcanobacterium pyogenes; foot rot (necrotic pododermatitis) and calf diphtheria caused by Fusobacterium necrophorum and metritis caused by Arcanobacterium pyogenes.

In Swine, BiloVet is indicated for use in the treatment of swine arthritis caused by Mycoplasma hyosynoviae; swine pneumonia caused by Pasteurella spp.; swine erysipelas caused by Erysipelothrix rhusiopathiae; swine dysentery associated with Treponema hyodysenteriae when followed by appropriate medication in the drinking water and/or feed.

Each mL contains 200 mg of tylosin activity (as tylosin base) in 50% propylene glycol with 4% benzyl alcohol, water for injection and hydrochloric acid for pH adjustment.

ADMINISTRATION AND DOSAGE: BiloVet is administered intramuscularly.

Use automatic syringe equipment only

BEEF CATTLE AND NON-LACTATING DAIRY CATTLE: Inject intramuscularly 8 mg per pound of body weight one time daily (1 mL per 25 pounds). Treatment should be continued 24 hours following remission of disease signs, not to exceed 5 days. Do not inject more than 10 mL per site.
SWINE: Inject intramuscularly 4 mg per pound of body weight (1 mL per 50 pounds) twice daily. Treatment should be continued 24 hours following remission of disease signs, not to exceed 3 days. Do not inject more than 5 mL per site.
Read accompanying directions fully before use.

CAUTION: Do not mix BiloVet with other injectable solutions as this may cause a precipitation of the active ingredients.

WARNINGS:

NOT FOR HUMAN USE.

KEEP OUT OF REACH OF CHILDREN.

Adverse reactions, including shock and death may result from overdosage in baby pigs.

Do not attempt injection into pigs weighing less than 25 pounds (0.5 mL) with the common syringe. It is recommended that tylosin 50 mg/mL injection be used in pigs weighing less than 25 lbs.

Do not administer to horses or other equines. Injection of tylosin in equines has been fatal.

RESIDUE WARNING:

Swine:

Swine intended for human consumption must not be slaughtered within 14 days of the last use of this drug.

RESIDUE WARNING:

Cattle:

Cattle intended for human consumption must not be slaughtered within 21 days of the last use of this drug product. This drug product is not approved for use in female dairy cattle 20 months of age or older, including dry dairy cows. Use in these cattle may cause drug residues in milk and/or in calves born to these cows. This product is not approved for use in calves intended to be processed for veal. A withdrawal period has not been established in pre-ruminating calves.

If tylosin medicated drinking water is used as a follow-up treatment for swine dysentery, the animal should thereafter receive feed containing 40 to 100 grams of tylosin per ton for 2 weeks to assure depletion of tissue residues.

STORAGE AND HANDLING

STORE AT 20°C-25°C (68°F -77°F). Use within 28 days of first puncture and puncture a maximum of 5 times with automatic syringe equipment. When using a draw-off spike or needle larger than 4-gauge, discard any product remaining in the vial immediately after use.

Approved by FDA under ANADA # 200-508

To report suspected adverse drug events, for technical assistance or to obtain a copy of the Safety Data Sheet (SDS), contact Bimeda, Inc. at 1-888-524-6332. For additional information about adverse drug experience reporting for animal drugs, contact FDA at 1-888-FDA-VETS, or www.fda.gov/reportanimalae.